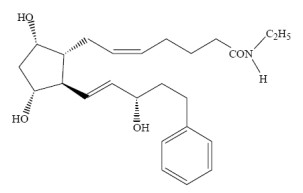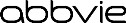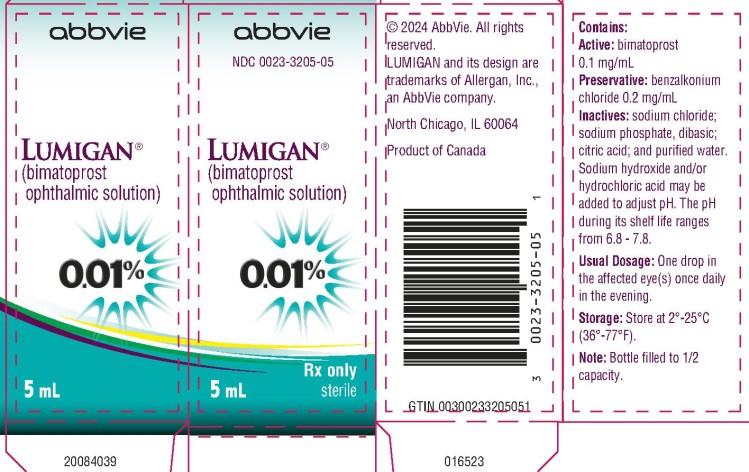 DRUG LABEL: LUMIGAN
NDC: 0023-3205 | Form: SOLUTION/ DROPS
Manufacturer: Allergan, Inc.
Category: prescription | Type: HUMAN PRESCRIPTION DRUG LABEL
Date: 20240601

ACTIVE INGREDIENTS: BIMATOPROST 0.1 mg/1 mL
INACTIVE INGREDIENTS: BENZALKONIUM CHLORIDE 0.2 mg/1 mL; SODIUM CHLORIDE; SODIUM PHOSPHATE, DIBASIC, UNSPECIFIED FORM; CITRIC ACID MONOHYDRATE; WATER

HIGHLIGHTS OF PRESCRIBING INFORMATION

These highlights do not include all the information needed to use LUMIGAN 0.01% safely and effectively. See full prescribing information for LUMIGAN 0.01%.
LUMIGAN® (bimatoprost ophthalmic solution) 0.01%, for topical ophthalmic use
Initial U.S. Approval: 2001

1 INDICATIONS AND USAGE

LUMIGAN® 0.01% is a prostaglandin analog indicated for the reduction of elevated intraocular pressure in patients with open angle glaucoma or ocular hypertension. (1)

2 DOSAGE AND ADMINISTRATION

One drop in the affected eye(s) once daily in the evening. (2)

3 DOSAGE FORMS AND STRENGTHS

Ophthalmic solution containing 0.1 mg/mL of bimatoprost. (3)

4 CONTRAINDICATIONS

Hypersensitivity. (4)

5 WARNINGS AND PRECAUTIONS

- Pigmentation: Pigmentation of the iris, periorbital tissue (eyelid) and eyelashes can occur. Iris pigmentation is likely to be permanent. (5.1)
- Eyelash Changes: Gradual change to eyelashes including increased length, thickness and number of lashes. Usually reversible. (5.2)

6 ADVERSE REACTIONS

Most common adverse reaction (31%) is conjunctival hyperemia. (6.1)

To report SUSPECTED ADVERSE REACTIONS, contact AbbVie at 1-800-678-1605 or FDA at 1-800-FDA-1088 or www.fda.gov/medwatch.

8 USE IN SPECIFIC POPULATIONS

Use in pediatric patients below the age of 16 years is not recommended because of potential safety concerns related to increased pigmentation following long-term chronic use. (8.4)

FULL PRESCRIBING INFORMATION

1 INDICATIONS AND USAGE

LUMIGAN® (bimatoprost ophthalmic solution) 0.01% is indicated for the reduction of elevated intraocular pressure in patients with open angle glaucoma or ocular hypertension.

2 DOSAGE AND ADMINISTRATION

The recommended dosage is one drop in the affected eye(s) once daily in the evening. LUMIGAN® (bimatoprost ophthalmic solution) 0.01% should not be administered more than once daily since it has been shown that more frequent administration of prostaglandin analogs may decrease the intraocular pressure lowering effect.

Reduction of the intraocular pressure starts approximately 4 hours after the first administration with maximum effect reached within approximately 8 to 12 hours.

LUMIGAN® 0.01% may be used concomitantly with other topical ophthalmic drug products to lower intraocular pressure. If more than one topical ophthalmic drug is being used, the drugs should be administered at least five (5) minutes apart.

3 DOSAGE FORMS AND STRENGTHS

Ophthalmic solution containing bimatoprost 0.1 mg/mL.

4 CONTRAINDICATIONS

LUMIGAN® 0.01% is contraindicated in patients with hypersensitivity to bimatoprost or to any of the ingredients [see Adverse Reactions (6.2)].

5 WARNINGS AND PRECAUTIONS

5.1 Pigmentation

Bimatoprost ophthalmic solution has been reported to cause changes to pigmented tissues. The most frequently reported changes have been increased pigmentation of the iris, periorbital tissue (eyelid) and eyelashes. Pigmentation is expected to increase as long as bimatoprost is administered. The pigmentation change is due to increased melanin content in the melanocytes rather than to an increase in the number of melanocytes. After discontinuation of bimatoprost, pigmentation of the iris is likely to be permanent, while pigmentation of the periorbital tissue and eyelash changes have been reported to be reversible in some patients. Patients who receive treatment should be informed of the possibility of increased pigmentation. The long term effects of increased pigmentation are not known.

Iris color change may not be noticeable for several months to years. Typically, the brown pigmentation around the pupil spreads concentrically towards the periphery of the iris and the entire iris or parts of the iris become more brownish. Neither nevi nor freckles of the iris appear to be affected by treatment. While treatment with LUMIGAN® (bimatoprost ophthalmic solution) 0.01% can be continued in patients who develop noticeably increased iris pigmentation, these patients should be examined regularly.

5.2 Eyelash Changes

LUMIGAN® 0.01% may gradually change eyelashes and vellus hair in the treated eye. These changes include increased length, thickness, and number of lashes. Eyelash changes are usually reversible upon discontinuation of treatment.

5.3 Intraocular Inflammation

Prostaglandin analogs, including bimatoprost, have been reported to cause intraocular inflammation. In addition, because these products may exacerbate inflammation, caution should be used in patients with active intraocular inflammation (e.g., uveitis).

5.4 Macular Edema

Macular edema, including cystoid macular edema, has been reported during treatment with bimatoprost ophthalmic solution. LUMIGAN® 0.01% should be used with caution in aphakic patients, in pseudophakic patients with a torn posterior lens capsule, or in patients with known risk factors for macular edema.

5.5 Bacterial Keratitis

There have been reports of bacterial keratitis associated with the use of multiple-dose containers of topical ophthalmic products. These containers had been inadvertently contaminated by patients who, in most cases, had a concurrent corneal disease or a disruption of the ocular epithelial surface.

5.6 Contact Lens Use

LUMIGAN® 0.01% contains benzalkonium chloride, which may be absorbed by and cause discoloration of soft contact lenses. Contact lenses should be removed prior to instillation of LUMIGAN® 0.01% and may be reinserted 15 minutes following its administration.

6 ADVERSE REACTIONS

The following adverse reactions are described elsewhere in the labeling:

- Pigmentation including blepharal pigmentation and iris hyperpigmentation [see Warnings and Precautions (5.1)]
- Eyelash Changes [see Warnings and Precautions (5.2)]
- Intraocular Inflammation [see Warnings and Precautions (5.3)]
- Macular Edema [see Warnings and Precautions (5.4)]
- Hypersensitivity [see Contraindications (4)]

6.1 Clinical Trials Experience

Because clinical trials are conducted under widely varying conditions, adverse reaction rates observed in the clinical trials of a drug cannot be directly compared to rates in the clinical trials of another drug and may not reflect the rates observed in practice.

In a 12-month clinical study with bimatoprost ophthalmic solutions 0.01%, the most common adverse reaction was conjunctival hyperemia (31%). Approximately 1.6% of patients discontinued therapy due to conjunctival hyperemia. Other adverse drug reactions (reported in 1 to 4% of patients) with LUMIGAN® 0.01% in this study included conjunctival edema, conjunctival hemorrhage, eye irritation, eye pain, eye pruritus, erythema of eyelid, eyelids pruritus, growth of eyelashes, hypertrichosis, instillation site irritation, punctate keratitis, skin hyperpigmentation, vision blurred, and visual acuity reduced.

6.2 Postmarketing Experience

The following adverse reactions have been identified during postapproval use of LUMIGAN® 0.01%. Because these reactions are reported voluntarily from a population of uncertain size, it is not always possible to reliably estimate their frequency or establish a causal relationship to drug exposure. These reactions, which have been chosen for inclusion due to either their seriousness, frequency of reporting, possible causal connection to LUMIGAN®, or a combination of these factors include: asthma-like symptoms, dizziness, dry eye, dyspnea, eye discharge, eye edema, foreign body sensation, headache, hypersensitivity including signs and symptoms of eye allergy and allergic dermatitis, hypertension, lacrimation increased, periorbital and lid changes associated with periorbital fat atrophy leading to skin tightness, deepening of the eyelid sulcus, eyelid ptosis, enophthalmos, and eyelid retraction; and photophobia.

8 USE IN SPECIFIC POPULATIONS

8.1 Pregnancy

Risk Summary

There are no adequate and well-controlled studies of LUMIGAN® (bimatoprost ophthalmic solution) 0.01% administration in pregnant women. There is no increase in the risk of major birth defects or miscarriages based on bimatoprost postmarketing experience.

In embryofetal developmental studies, administration of bimatoprost to pregnant mice and rats during organogenesis, resulted in abortion and early delivery at oral doses at least 33 times (mice) or 94 times (rats) the human exposure to bimatoprost 0.03% dosed bilaterally once daily (based on blood area under the curve [AUC] levels). These adverse effects were not observed at 2.6 times (mice) and 47 times (rats) the human exposure to bimatoprost 0.03% dosed bilaterally once daily (based on blood AUC levels).

In pre/postnatal development studies, administration of bimatoprost to pregnant rats from organogenesis to the end of lactation resulted in reduced gestation length and fetal body weight, and increased fetal and pup mortality at oral doses at least 41 times the human systemic exposure to bimatoprost 0.03% dosed bilaterally once daily (based on blood AUC levels). No adverse effects were observed in rat offspring at exposures estimated at 14 times the human exposure to bimatoprost 0.03% dosed bilaterally once daily (based on blood AUC levels).

Because animal reproductive studies are not always predictive of human response LUMIGAN® 0.01% should be administered during pregnancy only if the potential benefit justifies the potential risk to the fetus.

Data

Animal Data

In an embryofetal development rat study, abortion was observed in pregnant rats administered bimatoprost orally during organogenesis at 0.6 mg/kg/day (94 times the human systemic exposure to bimatoprost 0.03% dosed bilaterally once daily, based on AUC). The No Observed Adverse Effect Level (NOAEL) for abortion was 0.3 mg/kg/day (estimated at 47 times the human systemic exposure to bimatoprost 0.03% dosed bilaterally once daily, based on AUC). No abnormalities were observed in rat fetuses at doses up to 0.6 mg/kg/day.

In an embryofetal development mouse study, abortion and early delivery were observed in pregnant mice administered bimatoprost orally during organogenesis at doses greater than or equal to 0.3 mg/kg/day (33 times the human systemic exposure to bimatoprost 0.03% dosed bilaterally once daily, based on AUC). The NOAEL for abortion and early delivery was 0.1 mg/kg/day (2.6 times the human systemic exposure to bimatoprost 0.03% dosed bilaterally once daily, based on AUC). No abnormalities were observed in mouse fetuses at doses up to 0.6 mg/kg/day (72 times the human systemic exposure to bimatoprost 0.03% dosed bilaterally once daily, based on AUC).

In a pre/postnatal development study, treatment of pregnant rats with bimatoprost orally from gestation day 7 to lactation day 20 resulted in reduced gestation length, increased late resorptions, fetal deaths, and postnatal pup mortality, and reduced pup body weight at doses greater than or equal to 0.3 mg/kg/day. These effects were observed at exposures at least 41 times the human systemic exposure to bimatoprost 0.03% dosed bilaterally once daily, based on AUC. The NOAEL for postnatal development and mating performance of the offspring was 0.1 mg/kg/day (estimated at 14 times the human systemic exposure to bimatoprost 0.03% dosed bilaterally once daily, based on AUC).

8.2 Lactation

Risk Summary

It is not known whether topical ocular treatment with LUMIGAN® 0.01% could result in sufficient systemic absorption to produce detectable quantities in human milk. In animal studies, bimatoprost has been shown to be present in breast milk of lactating rats at an intravenous dose (i.e., 1 mg/kg) 970 times the RHOD (on a mg/rn 2 basis), however, no animal data is available at clinically relevant doses.

The developmental and health benefits of breastfeeding should be considered along with the mother’s clinical need for LUMIGAN® 0.01% and any potential adverse effects on the breastfed child from LUMIGAN® 0.01%.

8.4 Pediatric Use

Use in pediatric patients below the age of 16 years is not recommended because of potential safety concerns related to increased pigmentation following long-term chronic use.

8.5 Geriatric Use

No overall clinical differences in safety or effectiveness have been observed between elderly and other adult patients.

10 OVERDOSAGE

No information is available on overdosage in humans. If overdose with LUMIGAN® (bimatoprost ophthalmic solution) 0.01% occurs, treatment should be symptomatic.

In oral (by gavage) mouse and rat studies, doses up to 100 mg/kg/day did not produce any toxicity. This dose expressed as mg/m^2 is at least 210 times higher than the accidental dose of one bottle of LUMIGAN® 0.01% for a 10 kg child.

11 DESCRIPTION

LUMIGAN® (bimatoprost ophthalmic solution) 0.01% is a synthetic prostamide analog with ocular hypotensive activity. Its chemical name is (Z)-7-[(1R,2R,3R,5S)-3,5-Dihydroxy-2-[(1E,3S)-3-hydroxy-5-phenyl-1-pentenyl]cyclopentyl]-5-N-ethylheptenamide, and its molecular weight is 415.58. Its molecular formula is C25H37NO4. Its chemical structure is:

Bimatoprost is a powder, which is very soluble in ethyl alcohol and methyl alcohol and slightly soluble in water. LUMIGAN® 0.01% is a clear, isotonic, colorless, sterile ophthalmic solution with an osmolality of approximately 290 mOsmol/kg.

LUMIGAN® 0.01% contains Active: bimatoprost 0.1 mg/mL; Inactives: benzalkonium chloride 0.2 mg/mL; sodium chloride; sodium phosphate, dibasic; citric acid; and purified water. Sodium hydroxide and/or hydrochloric acid may be added to adjust pH. The pH during its shelf life ranges from 6.8-7.8.

12 CLINICAL PHARMACOLOGY

12.1 Mechanism of Action

Bimatoprost, a prostaglandin analog, is a synthetic structural analog of prostaglandin with ocular hypotensive activity. It selectively mimics the effects of naturally occurring substances, prostamides. Bimatoprost is believed to lower intraocular pressure (IOP) in humans by increasing outflow of aqueous humor through both the trabecular meshwork and uveoscleral routes. Elevated IOP presents a major risk factor for glaucomatous field loss. The higher the level of IOP, the greater the likelihood of optic nerve damage and visual field loss.

12.3 Pharmacokinetics

Absorption

After one drop of bimatoprost ophthalmic solution 0.03% was administered once daily to both eyes of 15 healthy subjects for two weeks, blood concentrations peaked within 10 minutes after dosing and were below the lower limit of detection (0.025 ng/mL) in most subjects within 1.5 hours after dosing. Mean Cmax and AUC0-24hr values were similar on days 7 and 14 at approximately 0.08 ng/mL and 0.09 ng•hr/mL, respectively, indicating that steady state was reached during the first week of ocular dosing. There was no significant systemic drug accumulation over time.

Distribution

Bimatoprost is moderately distributed into body tissues with a steady-state volume of distribution of 0.67 L/kg. In human blood, bimatoprost resides mainly in the plasma. Approximately 12% of bimatoprost remains unbound in human plasma.

Elimination

Metabolism

Bimatoprost is the major circulating species in the blood once it reaches the systemic circulation following ocular dosing. Bimatoprost then undergoes oxidation, N-deethylation and glucuronidation to form a diverse variety of metabolites.

Excretion

Following an intravenous dose of radiolabeled bimatoprost (3.12 mcg/kg) to six healthy subjects, the maximum blood concentration of unchanged drug was 12.2 ng/mL and decreased rapidly with an elimination half-life of approximately 45 minutes. The total blood clearance of bimatoprost was 1.5 L/hr/kg. Up to 67% of the administered dose was excreted in the urine while 25% of the dose was recovered in the feces.

13 NONCLINICAL TOXICOLOGY

13.1 Carcinogenesis, Mutagenesis, Impairment of Fertility

Carcinogenesis

Bimatoprost was not carcinogenic in either mice or rats when administered by oral gavage for 104 weeks at doses up to 2 mg/kg/day and 1 mg/kg/day, respectively (192 and 291 times the estimated human systemic exposure to bimatoprost 0.03% dosed bilaterally once daily, respectively, based on blood AUC levels)

Mutagenesis

Bimatoprost was not mutagenic or clastogenic in the Ames test, in the mouse lymphoma test, or in the in vivo mouse micronucleus tests.

Impairment of Fertility

Bimatoprost did not impair fertility in male or female rats up to doses of 0.6 mg/kg/day (at least 103 times the recommended human exposure to bimatoprost 0.03% dosed bilaterally once daily based on blood AUC levels).

14 CLINICAL STUDIES

In a 12-month clinical study of patients with open angle glaucoma or ocular hypertension with an average baseline IOP of 23.5 mmHg, the IOP-lowering effect of LUMIGAN® 0.01% once daily (in the evening) was up to 7.5 mmHg.

16 HOW SUPPLIED/STORAGE AND HANDLING

LUMIGAN® (bimatoprost ophthalmic solution) 0.01% is supplied sterile in opaque white low density polyethylene ophthalmic dispenser bottles and tips with turquoise polystyrene caps in the following sizes:

2.5 mL fill in a 5 mL container - NDC 0023-3205-03
5 mL fill in a 10 mL container - NDC 0023-3205-05
7.5 mL fill in a 10 mL container - NDC 0023-3205-08

Storage: Store at 2°C to 25°C (36°F to 77°F).

After opening, LUMIGAN® 0.01% can be used until the expiration date on the bottle.

17 PATIENT COUNSELING INFORMATION

Potential for Pigmentation

Advise patients about the potential for increased brown pigmentation of the iris, which may be permanent. Also inform patients about the possibility of eyelid skin darkening, which may be reversible after discontinuation of LUMIGAN® (bimatoprost ophthalmic solution) 0.01%.

Potential for Eyelash Changes

Inform patients of the possibility of eyelash and vellus hair changes in the treated eye during treatment with LUMIGAN® 0.01%. These changes may result in a disparity between eyes in length, thickness, pigmentation, number of eyelashes or vellus hairs, and/or direction of eyelash growth. Eyelash changes are usually reversible upon discontinuation of treatment.

Handling the Container

Instruct patients to avoid allowing the tip of the dispensing container to contact the eye, surrounding structures, fingers, or any other surface in order to avoid contamination of the solution by common bacteria known to cause ocular infections. Serious damage to the eye and subsequent loss of vision may result from using contaminated solutions.

When to Seek Physician Advice

Advise patients that if they develop an intercurrent ocular condition (e.g., trauma or infection), have ocular surgery, or develop any ocular reactions, particularly conjunctivitis and eyelid reactions, they should immediately seek their physician’s advice concerning the continued use of LUMIGAN® 0.01%.

Contact Lens Use

Advise patients that LUMIGAN® 0.01% contains benzalkonium chloride, which may be absorbed by soft contact lenses. Contact lenses should be removed prior to instillation of LUMIGAN® 0.01% and may be reinserted 15 minutes following its administration.

Use with Other Ophthalmic Drugs

Advise patients that if more than one topical ophthalmic drug is being used, the drugs should be administered at least five (5) minutes between applications.

Distributed by:
AbbVie Inc.
North Chicago, IL 60064

© 2024 AbbVie. All rights reserved.
LUMIGAN and its design are trademarks of Allergan, Inc., an AbbVie company.

v2.0USPI3205

PACKAGE LABEL

PRINCIPAL DISPLAY PANEL

NDC 0023-3205-05

abbvie
LUMIGAN®
(bimatoprost
ophthalmic solution)
0.01%
Rx only
5 mL sterile